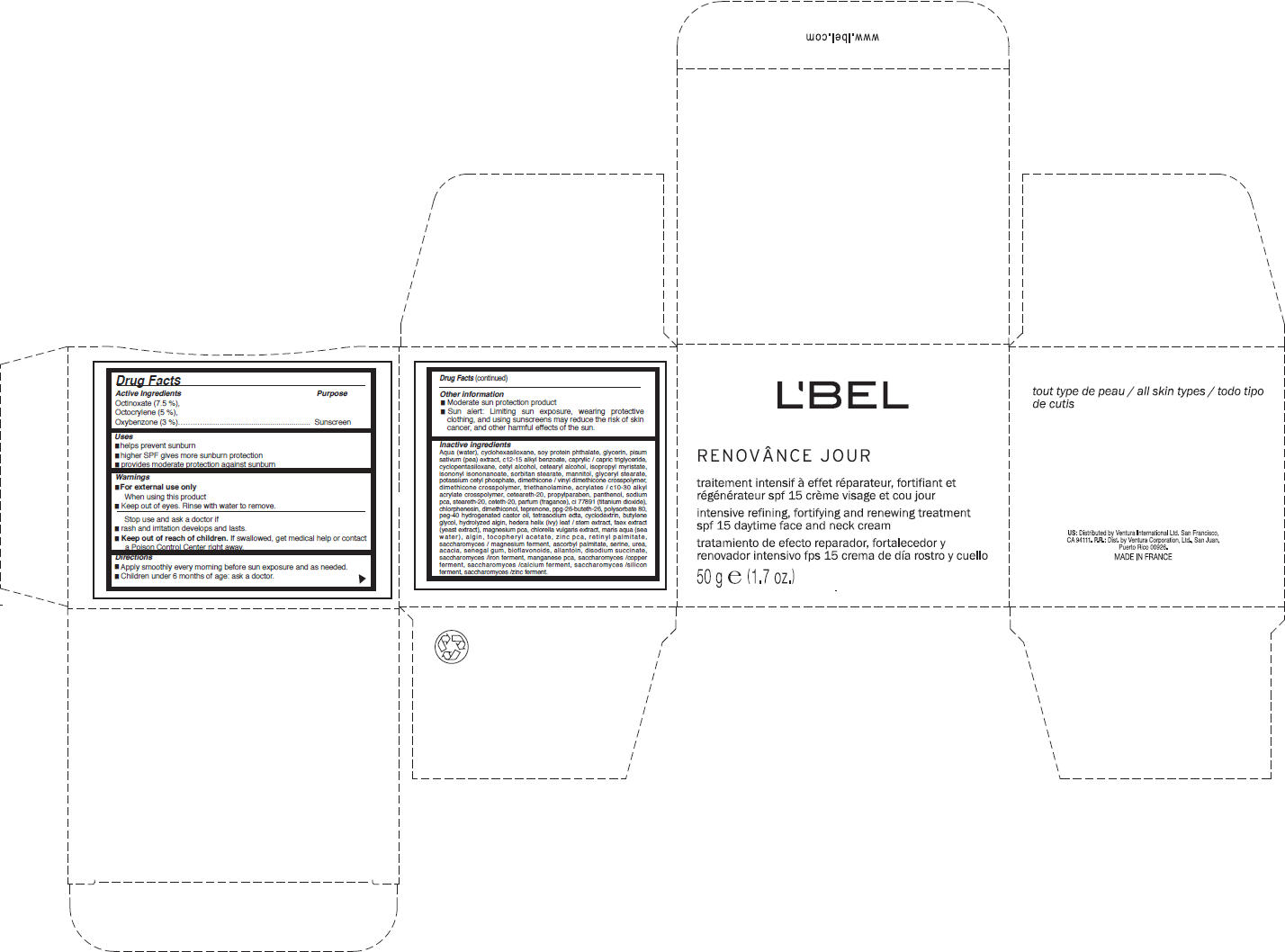 DRUG LABEL: LBel Paris 
NDC: 14783-038 | Form: CREAM
Manufacturer: Ventura International LTD
Category: otc | Type: HUMAN OTC DRUG LABEL
Date: 20100810

ACTIVE INGREDIENTS: Octinoxate 3.75 g/50 g; Octocrylene 2.5 g/50 g; Oxybenzone 1.5 g/50 g
INACTIVE INGREDIENTS: water; cyclomethicone 6; glycerin; snow pea; c12-15 alkyl benzoate; medium-chain triglycerides; cyclomethicone 5; cetyl alcohol; cetostearyl alcohol; isopropyl myristate; isononyl isononanoate; sorbitan monostearate; mannitol; glyceryl monostearate; potassium cetyl phosphate; trolamine; polyoxyl 20 cetostearyl ether; propylparaben; panthenol; sodium pyrrolidone carboxylate; steareth-20; ceteth-20; chlorphenesin; titanium dioxide; teprenone; polysorbate 80; polyoxyl 40 hydrogenated castor oil; edetate sodium; butylene glycol; kalmia latifolia leaf; yeast; vitamin a palmitate; ascorbyl palmitate; serine; urea; acacia; allantoin; sodium succinate anhydrous

L'BEL
RENOVÂNCE JOUR

Drug Facts

Active Ingredients

Octinoxate (7.5 %), Octocrylene (5 %), Oxybenzone (3 %)

Purpose

Sunscreen

Uses

- Helps prevent sunburn
- Higher SPF gives more sunburn protection
- Provides moderate protection against sunburn

Warnings

- For external use only.

When using this product

- keep out of eyes. Rinse with water to remove.

Stop use and ask a doctor if

- rash and irritation develops and lasts.

- Keep out of reach of children. If swallowed, get medical help or contact a Poison Control Center right away.

Directions

- Apply smoothly every morning before sun exposure and as needed.
- Children under 6 months of age: ask a doctor.

Other information

- Moderate sun protection product.
- Sun alert: Limiting sun exposure, wearing protective clothing, and using sunscreens may reduce the risk of skin cancer, and other harmful effects of the sun.

Inactive ingredients

Aqua (water), cyclohexasiloxane, soy protein phthalate, glycerin, pisum sativum (pea) extract, c12-15 alkyl benzoate, caprylic / capric triglyceride, cyclopentasiloxane, cetyl alcohol, cetearyl alcohol, isopropyl myristate, isononyl isononanoate, sorbitan stearate, mannitol, glyceryl stearate, potassium cetyl phosphate, dimethicone / vinyl dimethicone crosspolymer, dimethicone crosspolymer, triethanolamine, acrylates / c10-30 alkyl acrylate crosspolymer, ceteareth-20, propylparaben, panthenol, sodium pca, steareth-20, ceteth-20, parfum (fragance), ci 77891 (titanium dioxide), chlorphenesin, dimethiconol, teprenone, ppg-26-buteth-26, polysorbate 80, peg-40 hydrogenated castor oil, tetrasodium edta, cyclodextrin, butylene glycol, hydrolyzed algin, hedera helix (ivy) leaf / stem extract, faex extract (yeast extract), magnesium pca, chlorella vulgaris extract, maris aqua (sea water), algin, tocopheryl acetate, zinc pca, retinyl palmitate, saccharomyces / magnesium ferment, ascorbyl palmitate, serine, urea, acacia, senegal gum, bioflavonoids, allantoin, disodium succinate, saccharomyces /iron ferment, manganese pca, saccharomyces /copper ferment, saccharomyces /calcium ferment, saccharomyces /silicon ferment, saccharomyces /zinc ferment.

US: Distributed by Ventura International Ltd. San Francisco, CA 94111

PRINCIPAL DISPLAY PANEL - 50 g Jar Carton

L'BEL

RENOVÂNCE JOUR

intensive refining, fortifying and renewing treatment
spf 15 daytime face and neck cream

50 g e (1.7 oz.)